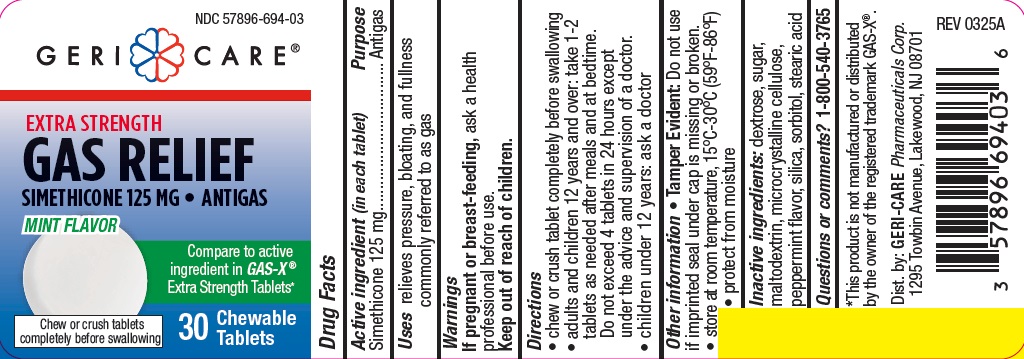 DRUG LABEL: EXTRA STRENGTH GAS RELIEF
NDC: 57896-694 | Form: TABLET, CHEWABLE
Manufacturer: Geri-Care Pharmaceuticals, Corp
Category: otc | Type: HUMAN OTC DRUG LABEL
Date: 20250428

ACTIVE INGREDIENTS: DIMETHICONE 125 mg/1 1
INACTIVE INGREDIENTS: SUCROSE; MALTODEXTRIN; SORBITOL; SILICON DIOXIDE; STEARIC ACID; DEXTROSE; MICROCRYSTALLINE CELLULOSE

GC 694

Active ingredient (in each tablet)

Simethicone 125 mg

Purpose

Antigas

Uses

relieves pressure, bloating, and fullness commonly referred to as gas

Warnings

If pregnant or breast feeding, ask a health professional before use.

Keep out of reach of children.

Directions

- chew or crush tablet completely before swallowing
- adults and children 12 years and over: take 1-2

tablets as needed after meals and at bedtime. Do
not exceed 4 tablets in 24 hours except under the
advice and supervision of a doctor.

- children under 12 years: ask a doctor

Other information

- Tamper Evident: Do not use if imprinted seal under cap is missing or broken.
- store at room temperature, 15°C-30°C (59°F-86°F)
- protect from moisture

Inactive ingredients

dextrose, sugar, maltodextrin, microcrystalline cellulose, peppermint flavor, silica, sorbitol, stearic acid

Questions or comments?

1-800-540-3765